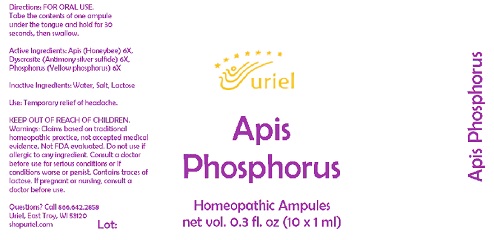 DRUG LABEL: Apis Phosphorus
NDC: 48951-1353 | Form: LIQUID
Manufacturer: Uriel Pharmacy Inc
Category: homeopathic | Type: HUMAN OTC DRUG LABEL
Date: 20211119

ACTIVE INGREDIENTS: PHOSPHORUS 6 [hp_X]/1 mL; APIS MELLIFERA 6 [hp_X]/1 mL; SILVER SULFIDE 6 [hp_X]/1 mL
INACTIVE INGREDIENTS: WATER; LACTOSE, UNSPECIFIED FORM; SODIUM CHLORIDE

Apis Phosphorus

INDICATIONS AND USAGE

Directions: FOR ORAL USE.

DOSAGE AND ADMINISTRATION

Take the contents of one ampule under the tongue and hold for 30 seconds, then swallow.

ACTIVE INGREDIENT

Active Ingredients: Apis (Honeybee) 6X, Dyscrasite (Antimony silver sulfide) 6X, Phosphorus (Yellow phosphorus) 6X

Inactive Ingredients: Water, Salt, Lactose

PURPOSE

Use: Temporary relief of headache.

KEEP OUT OF REACH OF CHILDREN.

WARNINGS

Warnings: Claims based on traditional homeopathic practice, not accepted medical evidence. Not FDA evaluated. Do not use if allergic to any ingredient. Consult a doctor before use for serious conditions or if conditions worse or persist. Contains traces of lactose. If pregnant or nursing, consult a doctor before use.

Questions? Call 866.642.2858
Uriel, East Troy, WI 53120
shopuriel.com